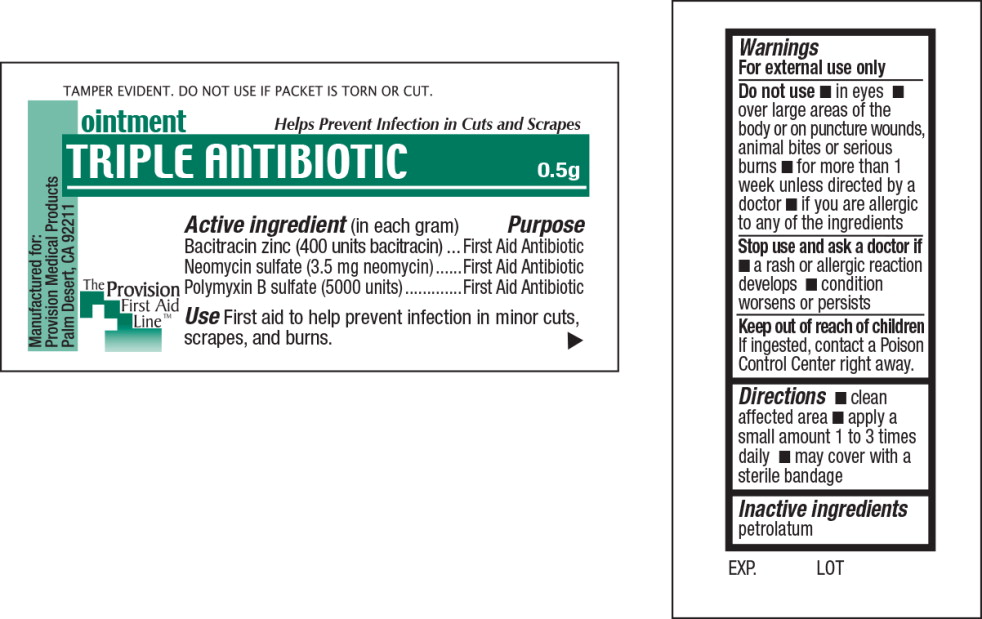 DRUG LABEL: Triple Antibiotic
NDC: 69103-5005 | Form: OINTMENT
Manufacturer: Provision Medical
Category: otc | Type: HUMAN OTC DRUG LABEL
Date: 20140829

ACTIVE INGREDIENTS: bacitracin zinc 400 [USP'U]/1 g; neomycin sulfate 3.5 mg/1 g; polymyxin b sulfate 5000 [USP'U]/1 g
INACTIVE INGREDIENTS: petrolatum

Active ingredient

(in each gram)

Bacitracin zinc (400 units bacitracin)

Neomycin sulfate (3.5 mg neomycin)

Polymyxin B sulfate (5000 units)

Purpose

First Aid Antibiotic

First Aid Antibiotic

First Aid Antibiotic

Use

First aid to help prevent infection in minor cuts, scrapes, and burns.

Warnings

For external use only

Do not use

- in eyes
- over large areas of the body or on puncture wounds, animal bites or serious burns
- for more than 1 week unless directed by a doctor
- if you are allergic to any of the ingredients

Stop use and ask a doctor if

- a rash or allergic reaction develops
- condition worsens or persists

Keep out of reach of children

If ingested, contact a Poison Control Center right away.

Directions

- clean affected area
- apply a small amount 1 to 3 times daily
- may cover with a sterile bandage

Inactive ingredients

petrolatum

Principal Display Panel - 0.5g Packet Label

TAMPER EVIDENT. DO NOT USE IF PACKET IS TORN OR CUT.

ointment

Helps Prevent Infection in Cuts and Scrapes

TRIPLE ANTIBIOTIC

0.5g

The Provision First Aid LineTM